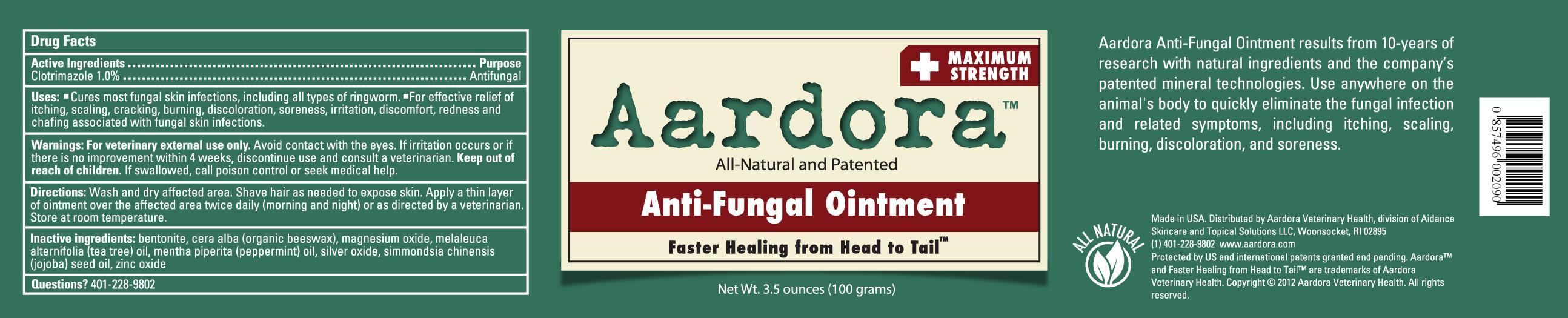 DRUG LABEL: Aardora Anti-Fungal
NDC: 24909-806 | Form: OINTMENT
Manufacturer: Aidance Skincare & Topical Solutions, LLC
Category: animal | Type: OTC ANIMAL DRUG LABEL
Date: 20121109

ACTIVE INGREDIENTS: CLOTRIMAZOLE 1.0 g/100 g
INACTIVE INGREDIENTS: BENTONITE; JOJOBA OIL; MAGNESIUM OXIDE; PEPPERMINT OIL; SILVER OXIDE; TEA TREE OIL; WHITE WAX; ZINC OXIDE

Drug Facts

Active Ingredient

Clotrimazole 1.0%

Purpose

Antifungal

Uses

- Cures most fungal skin infections, including all types of ringworm.
- For effective relief of itching, scaling, cracking, burning, discoloration, soreness, irritation, discomfort, redness and chafing associated with fungal skin infections.

Warnings

For veterinary external use only. Avoid contact with the eyes. If irritation occurs or if there is no improvement withing 4 weeks, discontinue use and consult a veterinarian.

Keep out of reach of children.

If swallowed, call poison control or seek medical help.

Directions

Wash and dry affected area. Shave hair as needed to expose skin. Apply a thin layer of ointment over the affected area twice daily (morning and night) or as directed by a veterinarian. Store at room temperature.

Inactive Ingredients

bentonite, cera alba (organic beeswax), magnesium oxide, melaleuca alternifolia (tea tree) oil, mentha piperita (peppermint) oil, silver oxide, simmondsia chinensis (jojoba) seed oil, zinc oxide

Questions? 401-228-9802

Aardora Anti-Fungal Ointment results from 10-years of research with natural ingredients and the company's patented mineral technologies. Use anywhere on the animal's body to quickly eliminate the fungal infection and related symptoms, including itching, scaling, burning, discoloration, and soreness.
Made in USA. Distributed by Aardora Veterinary Health, division of Aidance Skincare & Topical Solutions, LLC., Woonsocket, RI 02895.
(1) 401-228-9802 www.aardora.com
Protected by US and international patents granted and pending. Aardora™ and Faster Healing from Head to Tail™ are trademarks of Aardora Veterinary Health. Copyright (C) 2012 Aardora Veterinary Health. All rights reserved.

PRINCIPAL DISPLAY PANEL - 100g Jar

Aardora
Maximum Strength
All-Natural and Patented

Anti-Fungal Ointment
Faster Healing from Head to Tail™